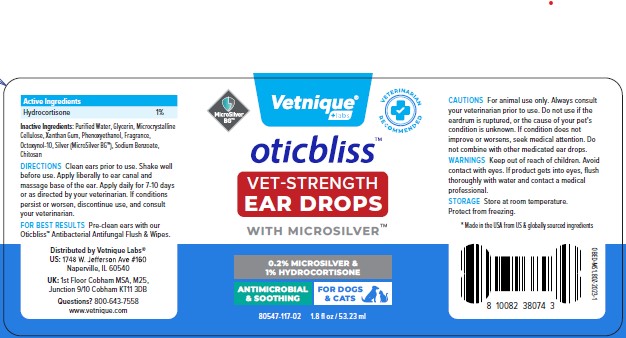 DRUG LABEL: OTICBLISS VET-STRENGTH EAR DROPS
NDC: 80547-117 | Form: SOLUTION
Manufacturer: Vetnique Labs Llc
Category: animal | Type: OTC ANIMAL DRUG LABEL
Date: 20230302

ACTIVE INGREDIENTS: HYDROCORTISONE 1 g/100 mL
INACTIVE INGREDIENTS: WATER; GLYCERIN; MICROCRYSTALLINE CELLULOSE 101; XANTHAN GUM; PHENOXYETHANOL; OCTOXYNOL-9; SODIUM BENZOATE; CHITOSAN LOW MOLECULAR WEIGHT (20-200 MPA.S)

VETNIQUE - OTICBLISS VET-STRENGTH EAR DROPS WITH MICROSILVER (80547-117)

Active Ingredients

HYDROCORTISONE 1%